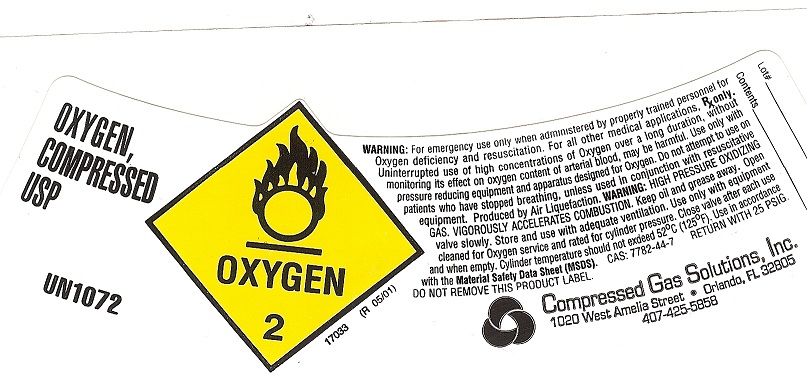 DRUG LABEL: Oxygen
NDC: 67596-111 | Form: GAS
Manufacturer: Compressed Gas Solutions Inc
Category: animal | Type: PRESCRIPTION ANIMAL DRUG LABEL
Date: 20170119

ACTIVE INGREDIENTS: OXYGEN 995 mL/1 L

Oxygen

PACKAGE LABEL

OXYGEN, COMPRESSED USP
UN1072
PRODUCED BY AIR LIQUEFACTION
OXYGEN 2
WARNING: For emergency use only when administered by properly trained personnel for oxygen deficiency and resuscitation. For all other medical applications. RX only. Uninterrupted use of high concentrations of oxygen over a long duration, without monitoring its effect on oxygen content of arterial blood, may be harmful. Do not attempt to use on patients who have stopped breathing unless used in conjunction with resuscitative equipment. Keep out of reach of children. Federal law requires that this container be refilled with oxygen USP only by establishments registered as a drug manufacturer in accordance with the Federal Food, Drug and Cosmetic Act. DANGER: MAY CAUSE OR INTENSIFY FIRE; OXIDIZER. CONTAINES GAS UNDER PRESSURE; MAY EXPLODE IF HEATHER. Do not handle until all safety precautions have been read and understood. Keep and store away from clothing and other combustible materials. Keep valves and fittings free from grease and oil. Use and store only outdoors or in a well-ventilated place. In case of fire: Stop leak if safe to do so. Use a back flow preventive device in the pipping. Use only with equipment of compatible materials of construction and rated for cylinder pressure. Use only with equipment cleaned for oxygen service. Open valve slowly. Close valve after each use and when empty. Protect from sunlight when ambient temperature exceeds 52 degrees C (125 degrees F). Read and follow the Safety Data Sheet (SDS) before use. CAS 7782-44-7 DO NOT REMOVE THIS PRODUCT LABEL.
COMPRESSED GAS SOLUTIONS, INC.
2450 SHADER RD
ORLANDO, FL 32804
407-293-3733